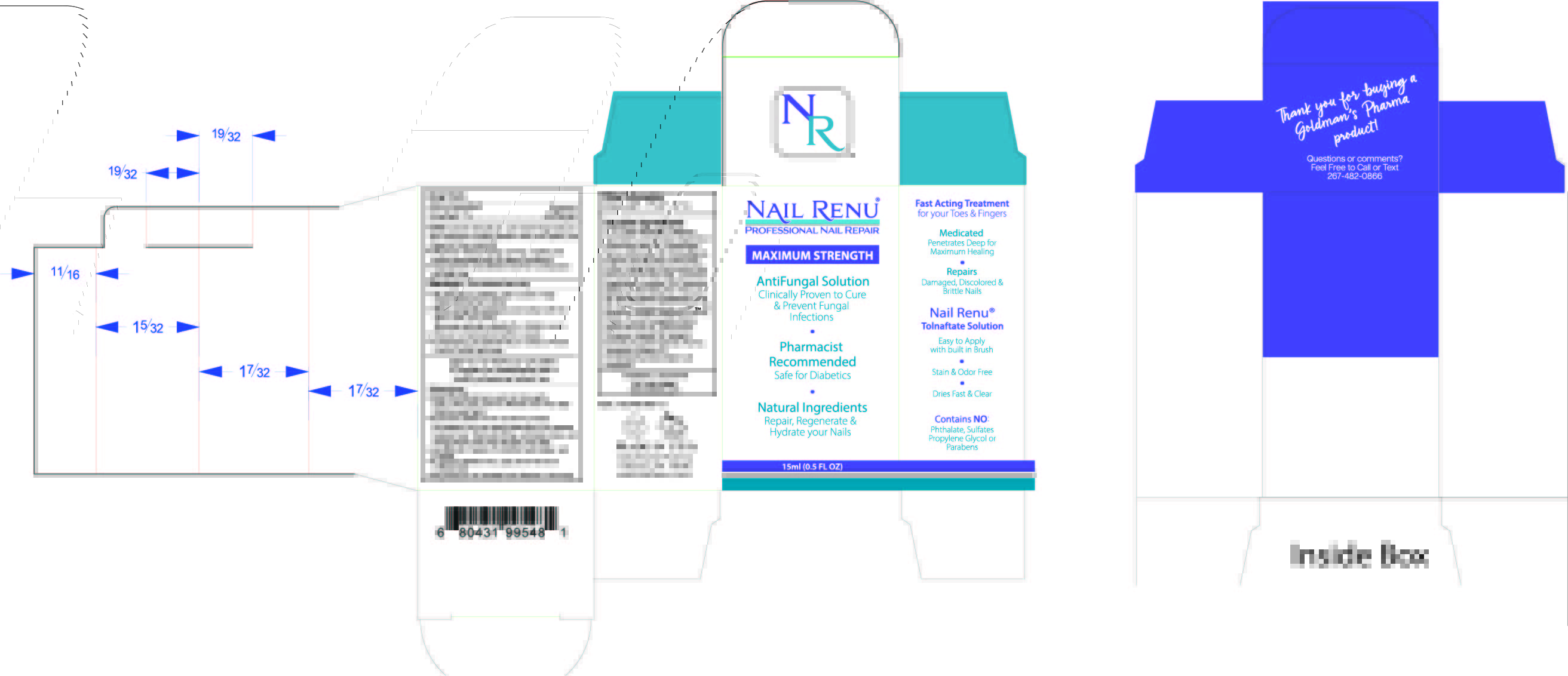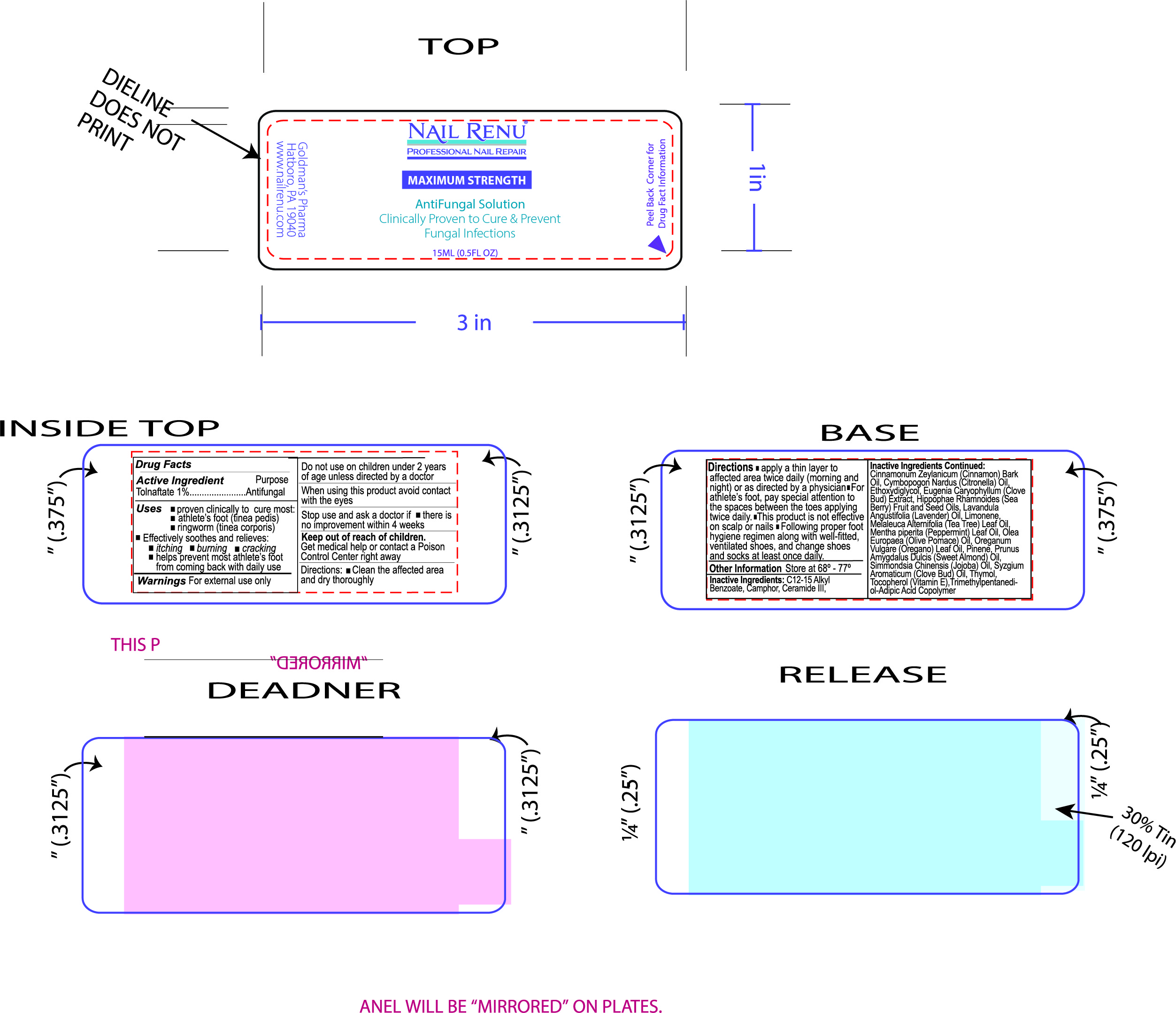 DRUG LABEL: Nail Renu
NDC: 76348-995 | Form: SOLUTION
Manufacturer: RENU LABORATORIES, INC.
Category: otc | Type: HUMAN OTC DRUG LABEL
Date: 20230322

ACTIVE INGREDIENTS: TOLNAFTATE 1 g/100 mL
INACTIVE INGREDIENTS: CERAMIDE 3; CAMPHOR (NATURAL); CLOVE OIL; THYMOL; CITRONELLA OIL; CLOVE; TEA TREE OIL; CINNAMON BARK OIL; TRIMETHYLPENTANEDIOL/ADIPIC ACID/GLYCERIN CROSSPOLYMER (25000 MPA.S); ALPHA-TOCOPHEROL; HIPPOPHAE RHAMNOIDES SEED OIL; HIPPOPHAE RHAMNOIDES FRUIT OIL; OREGANO LEAF OIL; LAVENDER OIL; LIMONENE, (+)-; ALKYL (C12-15) BENZOATE; PINENE; JOJOBA OIL; DIETHYLENE GLYCOL MONOETHYL ETHER; PEPPERMINT OIL; OLIVE OIL; ALMOND OIL

NAIL RENU ANTIFUNGAL SOLUTION

Purpose

Antifungal

Uses

- proven clinically to cure most Fungal nail and Skin infections including athlete's foot (tinea pedis) and ringworm (tinea corporis)
- Effectively relieves itching, burning, cracking and scaling associated with the above conditions.
- helps prevent most athlete's foot from coming back with daily use

Warnings

- For external use only.

- Do not use on children under 2 years of age unless directed by a doctor

- When using this product avoid contact with the eyes, nose, and mouth.

Stop use and ask a doctor if

- irritation occurs
- there is no improvement within 4 weeks
- if swallowed, get medical help or contact a Poison Control Center right away.

KEEP OUT OF REACH OF CHILDREN

PREGNANCY OR BREAST FEEDING

If Pregnant or breastfeeding ask a health professional before use.

Directions:

- clean the affected area and dry thoroughly
- apply a thin layer over the affected area twice daily (morning and night)
- supervise children in the use of this product
- for athlete's foot, pay special attention to the spaces between toes. Wear well-fitting, ventilated shoes, and change shoes and socks at least once daily
- use daily for 4 weeks. If condition lasts longer, ask a doctor
- to prevent athlete's foot, apply to the feet once or twice daily
- this product is not intended for/or effective on the scalp.

Other information

- Store at 68º - 77º (20º - 25º C)

Questions or Comments

267-482-0866

www.nailrenu.com

Inactive Ingredients

C12-15 Alkyl Benzoate, Camphor, Ceramide III, Cinnamonum Zeylanicum (Cinnamon) Bark Oil, Cymbopogon Nardus (Citronella) Oil, Ethoxydiglycol, Eugenia Caryophyllum (Clove) Bud Extract, Hippophae Rhamnoides (Sea Berry) Fruit and Seed Oils, Lavandula Angustifolia (Lavender) Oil, Limonene, Melaleuca Alternifolia (Tea Tree) Leaf Oil, Mentha piperita (Peppermint) Leaf Oil, Olea Europaea (Olive Pomace) Oil, Oreganum Vulgare (Oregano) Leaf Oil, Pinene, Prunus Amygdallus Dulcis (Sweet Almond) Oil, Simmondsia Chinensis (Jojoba) Oil, Syzgium Aromatique (Clove) Bud Oil, Thymol, Tocopherol (Vitamin E), Trimethylpentanediol-Adipic Acid Copolymer

Directions

- clean the affected area and dry thoroughly
  apply a thin layer over the affected area twice daily (morning and night)

ACTIVE INGREDIENT

Tolnaftate

Nail RENU LABEL ART

AND

NAIL RENU

BOX ART